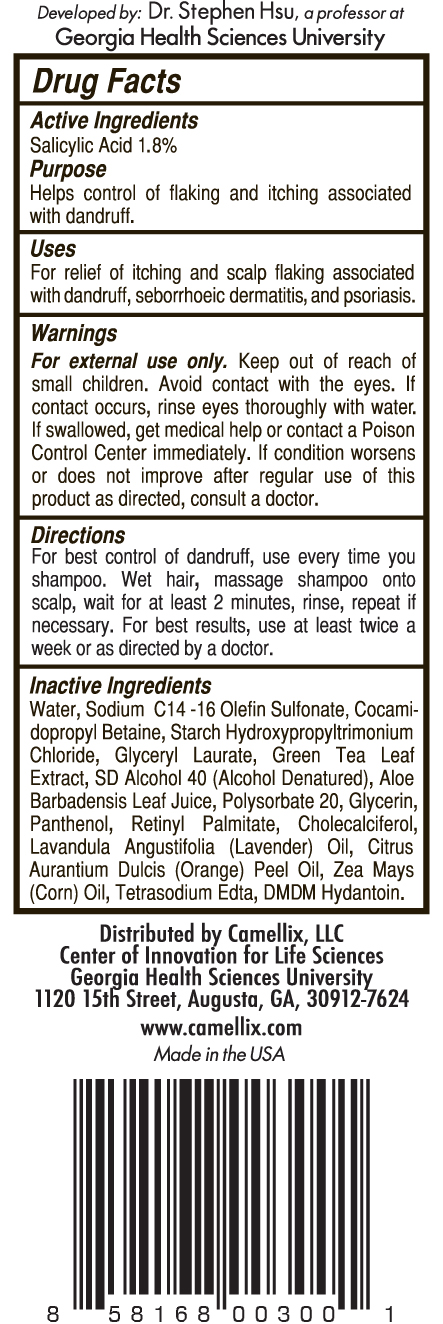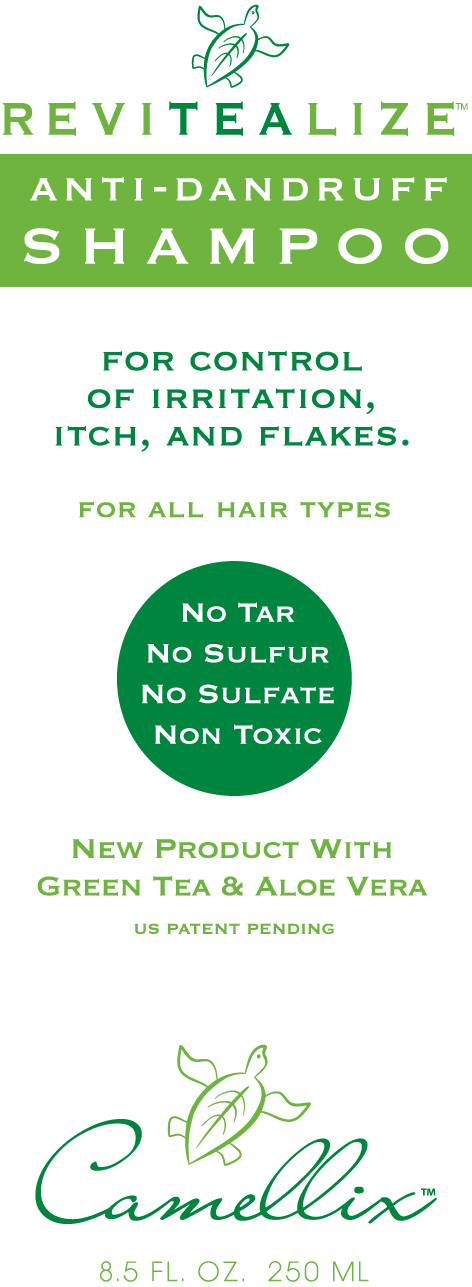 DRUG LABEL: REVITEALIZE
NDC: 54866-000 | Form: SHAMPOO
Manufacturer: Camellix, LLC
Category: otc | Type: HUMAN OTC DRUG LABEL
Date: 20120124

ACTIVE INGREDIENTS: Salicylic Acid 18 mg/1 mL
INACTIVE INGREDIENTS: WATER; SODIUM C14-16 OLEFIN SULFONATE ; COCAMIDOPROPYL BETAINE; GLYCERYL LAURATE; GREEN TEA LEAF; ALCOHOL; ALOE VERA LEAF ; POLYSORBATE 20; GLYCERIN; PANTHENOL; VITAMIN A PALMITATE; CHOLECALCIFEROL; LAVENDER OIL ; ORANGE OIL; CORN OIL; EDETATE SODIUM; DMDM HYDANTOIN

Drug Facts

Active Ingredients:

Salicylic Acid 1.8%

Purpose:

Help Control of flaking and itching associated with dandruff

Uses:

For relief of itching and scalp flaking associated with dandruff, seborrheic dermatitis and psoriasis.

Warnings:

- For external use only.

KEEP OUT OF REACH OF CHILDREN

Keep out of reach of small children. Avoid contact with the eyes. If contact occurs, rinse eyes thoroughly with water.

ASK DOCTOR

If swallowed, get medical help or contact a Poison Control Center immediately. If condition worsens or does not improve after regular use of this product as directed, consult a doctor.

Directions
For best control of dandruff, use every time you shampoo. Wet hair, massage shampoo onto scalp, wait for at least 2 minutes, rinse, repeat if necessary.
For best results use at least twice a week or as directed by a doctor

Inactive Ingredients
Water, Sodium C14-16 Olefin Sulfonate, Cocamidopropyl Betaine, Stach Hydroxypropyltrimonium Chloride, Glycerol Laurate, Green Tea Leaf Extract, SD Alcohol 40 (Alcohol Denatured), Aloe barbadensis Leaf Juice, Polysorbate 20, Glycerin, Panthenol, Retinyl Palmitate, Cholecalciferol, Lavandula Angustifolia (Lavender) Oil, Citrus Aurantium Dulcis (Orange) Peel Oil, Zea Mays (Corn) Oil, Tetrasodium EDTA, DMDM Hydantoin.